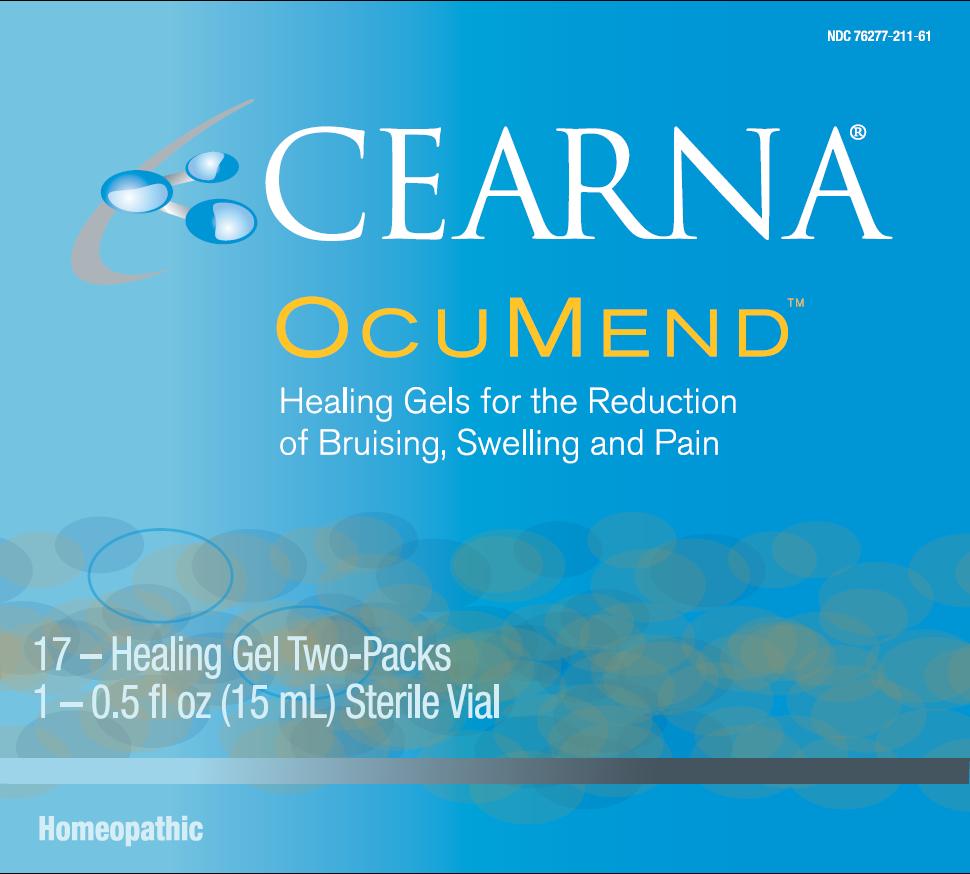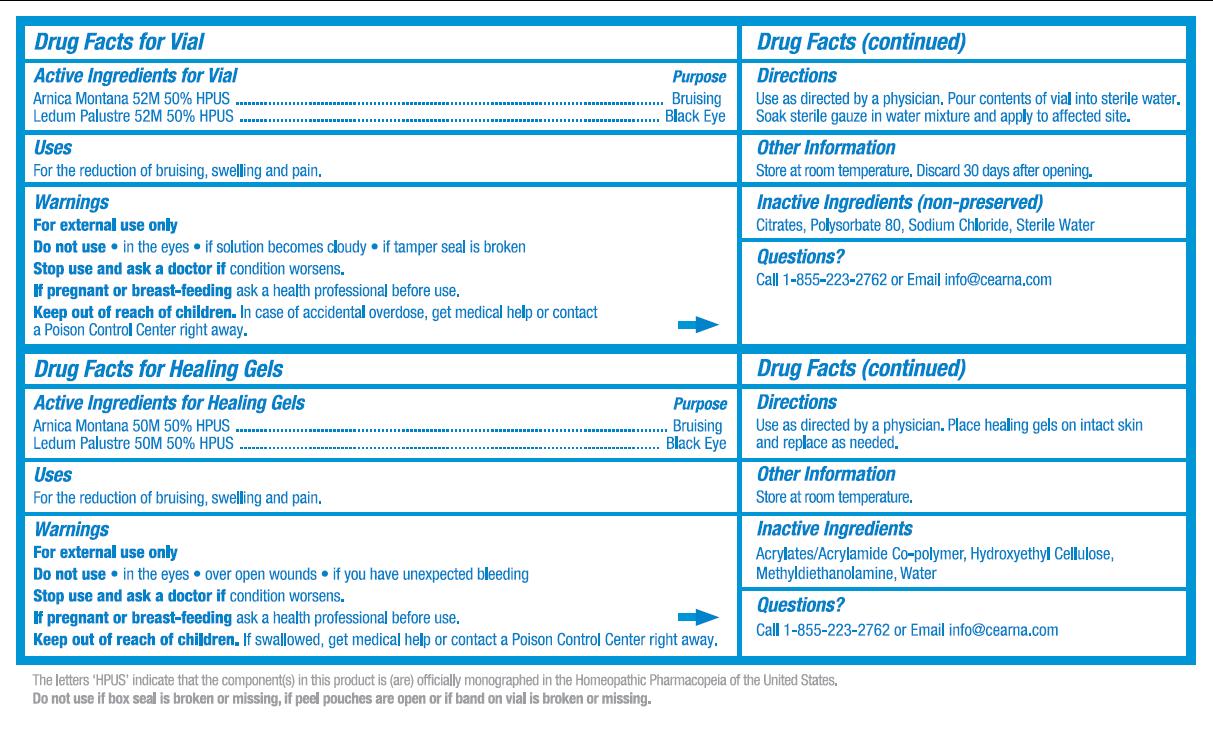 DRUG LABEL: OcuMend
NDC: 76277-211 | Form: KIT | Route: TOPICAL
Manufacturer: Cearna, Inc.
Category: homeopathic | Type: HUMAN OTC DRUG LABEL
Date: 20120308

ACTIVE INGREDIENTS: ARNICA MONTANA 52 [hp_M]/1 1; LEDUM PALUSTRE TWIG 52 [hp_M]/1 1; ARNICA MONTANA 52 [hp_M]/15 mL; LEDUM PALUSTRE TWIG 52 [hp_M]/15 mL
INACTIVE INGREDIENTS: METHYL DIETHANOLAMINE; WATER; POLYSORBATE 80; SODIUM CHLORIDE; WATER

Active Ingredients for Vial:

Arnica Montana 52M 50% HPUS

Ledum Palustre 52M 50% HPUS

Active Ingredients for Healing Gels:
Arnica Montana 52M 50% HPUS

Ledum Palustre 52M 50% HPUS

Purpose for Vial:

Arnica Montana 52M 50% HPUS .................................... Bruising

Ledum Palustre 52M 50% HPUS ..................................Black Eye

Purpose for Healing Gels:

Arnica Montana 52M 50% HPUS .................................... Bruising

Ledum Palustre 52M 50% HPUS ..................................Black Eye

INDICATIONS AND USAGE

Uses for Vial:

For the reduction of bruising, swelling and pain.

Uses for Healing Gels:

For the reduction of bruising, swelling and pain.

Warnings for Vial:

For external use only

Warnings for Healing Gels:

For external use only

Do not use for Vial:

Do not use

- in the eyes
- if solution becomes cloudy
- if tamper seal is broken

Do not use for Healing Gels:
Do not use

- in the eyes
- over open wounds
- if you have unexpected bleeding

Stop use for Vial:

Stop use and ask a doctor if condition worsens.

Stop use for Healing Gels:

Stop use and ask a doctor if condition worsens.

Pregnancy Warning for Vial:

If pregnant or breast-feeding ask a health professional before use.

Pregnancy Warning for Healing Gels:

If pregnant or breast-feeding ask a health professional before use.

Children Section for Vial:

Keep out of reach of children. In case of accidental overdose, get medical help or contact a Poison Control Center right away.

Children Section for Healing Gels:

Keep out of reach of children. In case of accidental overdose, get medical help or contact a Poison Control Center right away.

DOSAGE AND ADMINISTRATION

Directions for Vial:

Use as directed by a physician. Pour contents of vial into sterile water. Soak sterile gauze in water mixture and apply to affected site.

Directions for Healing Gels:

Use as directed by a physician. Place healing gels on intact skin and replace as needed.

Other information for Vial:

Store at room temperature. Discard 30 days after opening.

Other information for Healing Gels:

Store at room temperature.

Inactive Ingredients (non-preserved) for Vial:

Citrates, Polysorbate 80, Sodium Chloride, Sterile Water

Inactive Ingredients for Healing Gels:

Acrylates/Acrylamide Co-polymer, Hydroxyethyl Cellulose, Methyldiethanolamine, Water

Questions for Vial:

Call 1-855-223-2762 or Email info@cearna.com

Questions for Healing Gels:

Call 1-855-223-2762 or Email info@cearna.com

DESCRIPTION

The letters HPUS indicate that the component(s) in this product is (are) officially monographed in the Homeopathic Pharmacopeia of the United States.

Do not use if box seal is broken or missing, if peel pouches are open or if band on vial is broken or missing.